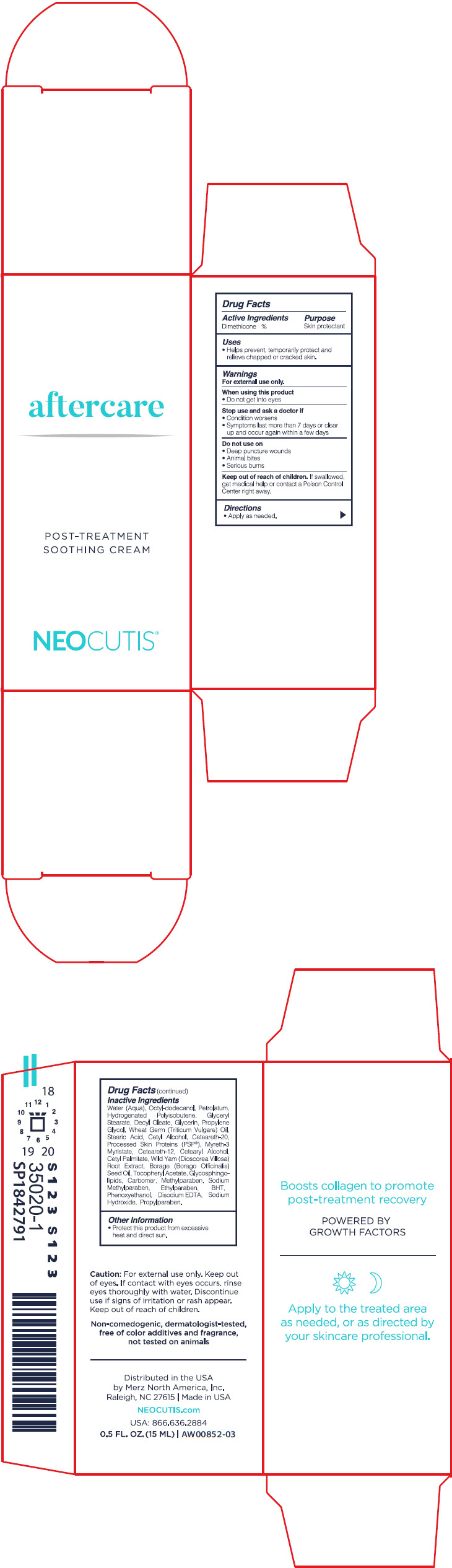 DRUG LABEL: AFTER CARE
NDC: 46783-004 | Form: CREAM
Manufacturer: Merz North America
Category: otc | Type: HUMAN OTC DRUG LABEL
Date: 20241101

ACTIVE INGREDIENTS: DIMETHICONE 4 mg/1 mL
INACTIVE INGREDIENTS: WATER; OCTYLDODECANOL; PETROLATUM; HYDROGENATED POLYISOBUTENE (1300 MW); GLYCERYL MONOSTEARATE; DECYL OLEATE; GLYCERIN; PROPYLENE GLYCOL; WHEAT GERM OIL; STEARIC ACID; CETYL ALCOHOL; POLYOXYL 20 CETOSTEARYL ETHER; HUMAN SKIN PROTEINS, PARTIALLY HYDROLYZED; MYRETH-3 MYRISTATE; CETEARETH-12; CETOSTEARYL ALCOHOL; CETYL PALMITATE; DIOSCOREA VILLOSA TUBER; BORAGE SEED OIL; .ALPHA.-TOCOPHEROL ACETATE; CARBOMER HOMOPOLYMER, UNSPECIFIED TYPE; METHYLPARABEN; METHYLPARABEN SODIUM; ETHYLPARABEN; BUTYLATED HYDROXYTOLUENE; PHENOXYETHANOL; EDETATE DISODIUM ANHYDROUS; SODIUM HYDROXIDE; PROPYLPARABEN

AFTER CARE

Drug Facts

Active ingredients

Dimethicone 4%

Purpose

Skin protectant

Uses

- Helps prevent, temporarily protect and relieve chapped or cracked skin.

Warnings

For external use only.

When using this product

- Do not get into eyes

Stop use and ask a doctor if

- Condition worsens
- Symptoms last more than 7 days or clear up and occur again within a few days

Do not use on

- Deep or puncture wounds
- Animal bites
- Serious burns

Keep out of reach of children. If swallowed, get medical help or contact a Poison Control Center right away.

Directions

- Apply as needed.

Inactive ingredients

Water (Aqua), Octyl-Dodecanol, Petrolatum, Hydrogenated Polyisobutene, Glyceryl Stearate, Decyl Oleate, Glycerin, Propylene Glycol, Wheat Germ (Triticum Vulgare) Oil, Stearic Acid, Cetyl Alcohol, Ceteareth-20, Processed Skin Proteins (PSP(R)), Myreth-3 Myristate, Ceteareth-12, Cetearyl Alcohol, Cetyl Palmitate, Wild Yam (Dioscorea Villosa) Root Extract, Borage (Borago Officinalis) Seed Oil, Tocopheryl Acetate, Glycosphingolipids, Carbomer, Methylparaben, Sodium Methylparaben, Ethylparaben, BHT, Phenoxyethanol, Disodium EDTA, Sodium Hydroxide, Propylparaben.

Other information

- Protect this product from excessive heat and direct sun.

Distributed in the USA
by Merz North America, Inc.
Raleigh, NC 27615

PRINCIPAL DISPLAY PANEL - 15 ML Bottle Carton

aftercare

POST-TREATMENT
SOOTHING CREAM

NEOCUTIS®